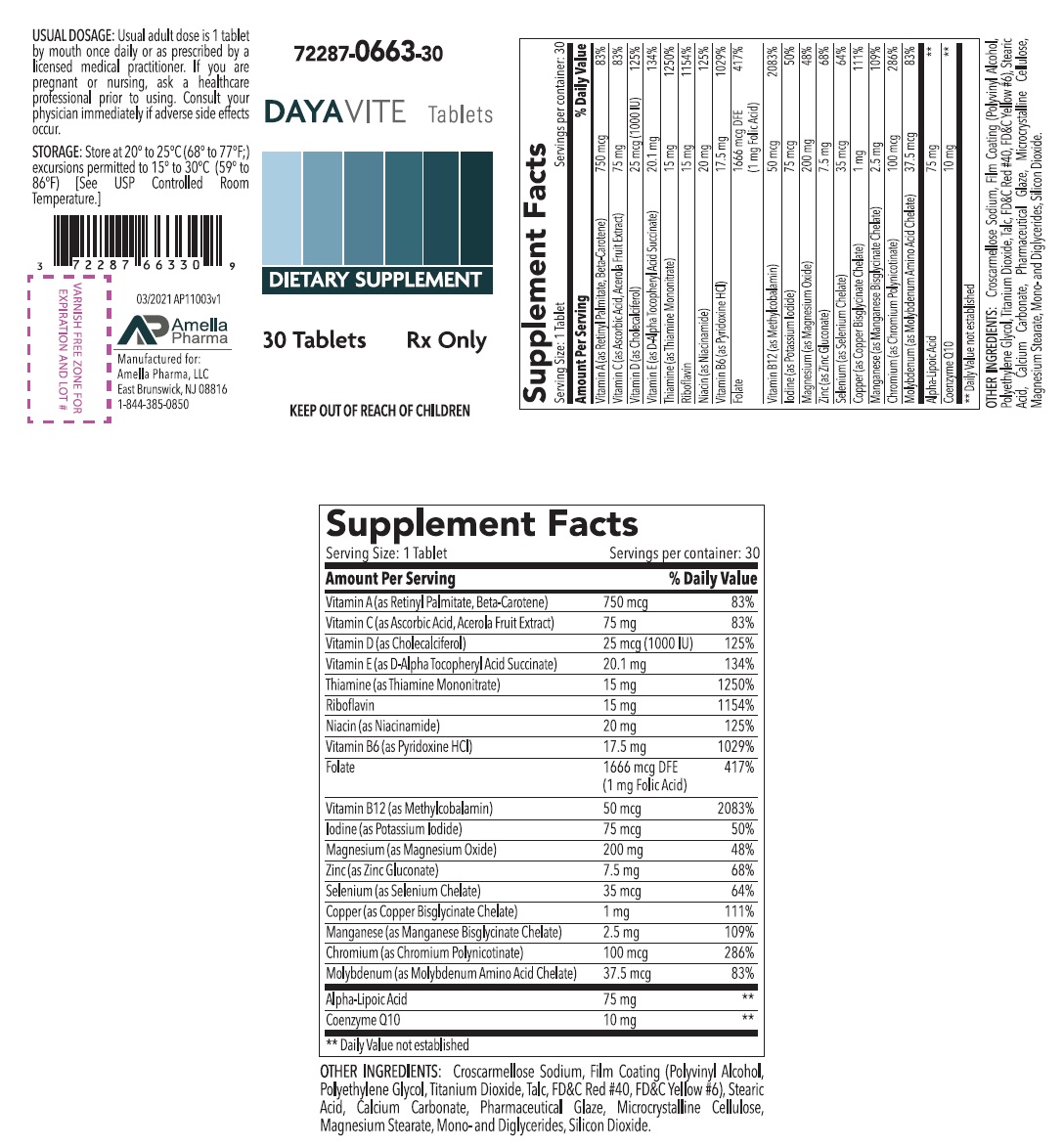 DRUG LABEL: Dayavite
NDC: 72287-663 | Form: TABLET, COATED
Manufacturer: Amella Pharma, Llc
Category: other | Type: DIETARY SUPPLEMENT
Date: 20210415

ACTIVE INGREDIENTS: VITAMIN A PALMITATE 750 ug/1 1; ASCORBIC ACID 75 mg/1 1; CHOLECALCIFEROL 25 ug/1 1; .ALPHA.-TOCOPHEROL SUCCINATE, D- 20.1 mg/1 1; THIAMINE MONONITRATE 15 mg/1 1; RIBOFLAVIN 15 mg/1 1; NIACINAMIDE 20 mg/1 1; PYRIDOXINE HYDROCHLORIDE 17.5 mg/1 1; FOLIC ACID 1 mg/1 1; METHYLCOBALAMIN 50 ug/1 1; POTASSIUM IODIDE 75 ug/1 1; MAGNESIUM OXIDE 200 mg/1 1; ZINC GLUCONATE 7.5 mg/1 1; SELENIUM 35 ug/1 1; COPPER 1 mg/1 1; MANGANESE 2.5 mg/1 1; CHROMIUM NICOTINATE 100 ug/1 1; MOLYBDENUM 37.5 ug/1 1; ALPHA LIPOIC ACID 75 mg/1 1; UBIDECARENONE 10 mg/1 1
INACTIVE INGREDIENTS: CROSCARMELLOSE SODIUM; POLYVINYL ALCOHOL, UNSPECIFIED; POLYETHYLENE GLYCOL, UNSPECIFIED; TITANIUM DIOXIDE; TALC; FD&C RED NO. 40; FD&C YELLOW NO. 6; STEARIC ACID; CALCIUM CARBONATE; SHELLAC; MICROCRYSTALLINE CELLULOSE; MAGNESIUM STEARATE; GLYCERYL MONO AND DIPALMITOSTEARATE; SILICON DIOXIDE

DAYAVITE

HEALTH CLAIM: DAYAVITE Tablets Dietary Supplement Dispensed by Prescription†

Supplement Facts
Serving Size:1 Tablet |  | Serving per container: 30
Amount Per Serving |  | % Daily Value
Vitamin A (as Retinyl Palmitate, Beta-Carotene) | 750 mcg | 83%
Vitamin C (as Ascorbic Acid, Acerola Fruit Extract) | 75 mg | 83%
Vitamin D (as Cholecalciferol) | 25 mcg (1000 IU) | 125%
Vitamin E (as D-Alpha Tocopheryl Acid Succinate) | 20.1 mg | 134%
Thiamine (as Thiamine Mononitrate) | 15 mg | 1250%
Riboflavin | 15 mg | 1154%
Niacin (as Niacinamide) | 20 mg | 125%
Vitamin B6 (as Pyridoxine HCl) | 17.5 mg | 1029%
Folate | 1666 mcg DFE | 417%
 | (1 mg Folic Acid)
Vitamin B12 (as Methylcobalamin) | 50 mcg | 2083%
Iodine (as Potassium Iodide) | 75 mcg | 50%
Magnesium (as Magnesium Oxide) | 200 mg | 48%
Zinc (as Zinc Gluconate) | 7.5 mg | 68%
Selenium (as Selenium Chelate) | 35 mcg | 64%
Copper (as Copper Bisglycinate Chelate) | 1 mg | 111%
Manganese (as Manganese Bisglycinate Chelate) | 2.5 mg | 109%
Chromium (as Chromium Polynicotinate) | 100 mcg | 286%
Molybdenum (as Molybdenum Amino Acid Chelate) | 37.5 mcg | 83%
Alpha-Lipoic Acid | 75 mg | **
Coenzyme Q10 | 10 mg | **
** Daily Value not established

OTHER INGREDIENTS: Croscarmellose Sodium, Film Coating (Polyvinyl Alcohol, Polyethylene Glycol, Titanium Dioxide, Talc, FD&C Red #40, FD&C Yellow #6), Stearic Acid, Calcium Carbonate, Pharmaceutical Glaze, Microcrystalline Cellulose, Magnesium Stearate, Mono-and Diglycerides, Silicon Dioxide.

DESCRIPTION

DAYAVITE Tablets is an orally administered prescription vitamin formulation for the clinical dietary management of suboptimal nutritional status in patients where advanced folate supplementation is required and nutritional supplementation in physiologically stressful conditions for maintenance of good health is needed.

DAYAVITE is a long, oblong, dark pink, clear-coated tablet, with debossed "A3” on one side.

PRECAUTIONS

CONTRAINDICATIONS
This product is contraindicated in patients with known hypersensitivity to any of the ingredients.

PRECAUTIONS
This product is contraindicated in patients with a known hypersensitivity to any of the ingredients.

DAYAVITE Tablets should only be used under the direction and supervision of a licensed medical practitioner. Use with caution in patients that may have a medical condition, are pregnant, lactating, trying to conceive, under the age of 18, or taking medications.

Folic acid supplementation may obscure pernicious anemia, in that hematologic remission can occur while neurological manifestations progress.

WARNINGS

KEEP OUT OF REACH OF CHILDREN.

Pregnancy and Lactation:
DAYAVITE Tablets is not intended for use in pregnant or lactating patients.

ADVERSE REACTIONS
Allergic sensitizations have been reported following oral administration of folic acid. Consult your physician immediately if adverse side effects occur.

DOSAGE AND ADMINISTRATION

Usual adult dose is 1 tablet by mouth once daily or as prescribed by a licensed medical practitioner.

HOW SUPPLIED HEALTH CLAIM:

DAYAVITE Tablets are supplied as a long, oblong, dark pink, clear-coated tablet, with debossed "A3” on one side.
DAYAVITE Tablets is available as the following:
72287-0663-30* 30ct bottle

Store at 20° to 25°C (68° to 77°F; excursions permitted to 15° to 30°C (59° to 86°F) [See USP Controlled Room Temperature]

Manufactured for:
Amella Pharma, LLC
E Brunswick, NJ 08816

Call your doctor for medical advice about side effects. You may report side effects to Amella Pharma, LLC at 1-844-385-0850.

Issued: 04/2021 AP11002v1

*Amella Pharma does not represent these product codes to be National Drug Codes (NDC). Product codes are formatted according to standard industry practice, to meet the formatting requirement by pedigree reporting and supply-chain control including pharmacies.

† This product is a prescription-folate with or without other dietary ingredients that – due to increased folate levels increased risk associated with masking of B12 deficiency (pernicious anemia) requires administration under the care of a licensed medical practitioner (61 FR 8760). The most appropriate way to ensure pedigree reporting consistent with these regulatory guidelines and safety monitoring is to dispense this product only by prescription (Rx). This is not an Orange Book product. This product may be administered only under a physician’s supervision and all prescriptions using this product shall be pursuant to state statutes as applicable. The ingredients, indication or claims of this product are not to be construed to be drug claims.

1. Federal Register Notice of August 2, 1973 (38 FR 20750)
2. Federal Register Notice of October 17, 1980 (45 FR 69043, 69044)
3. Federal Register Notice of March 5, 1996 (61 FR 8760)